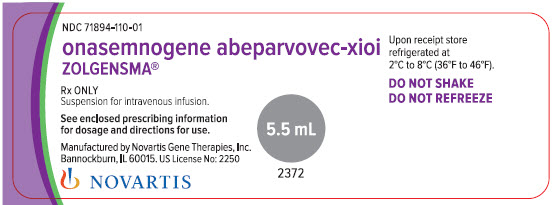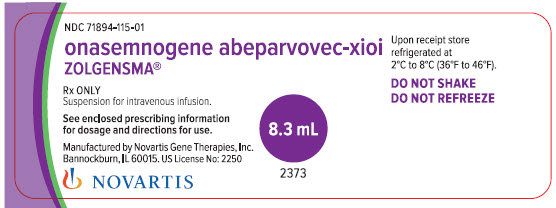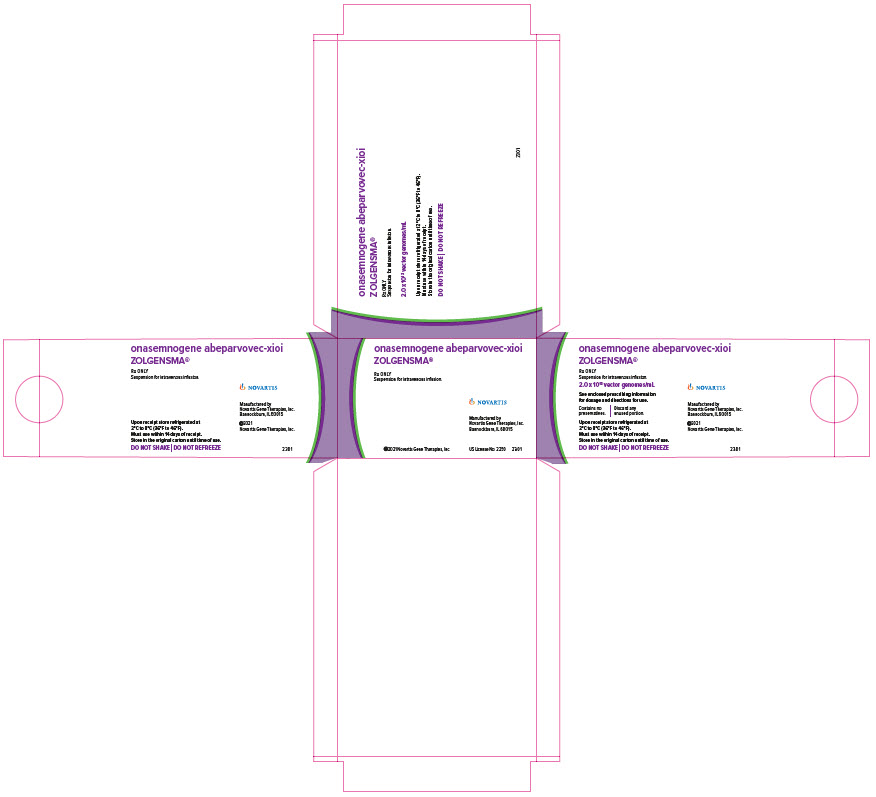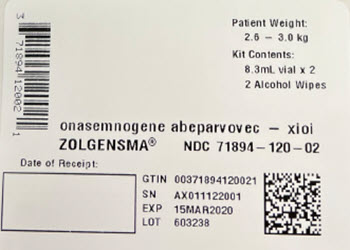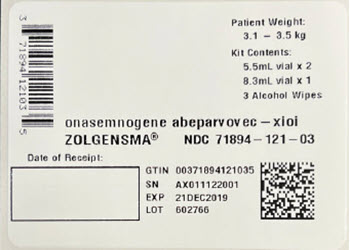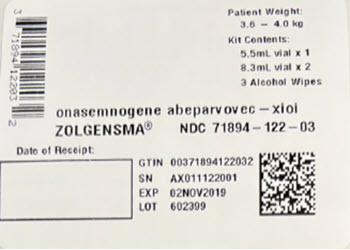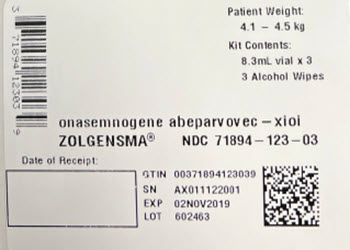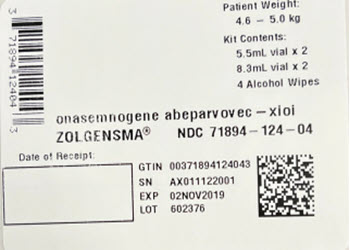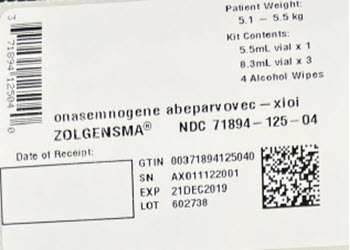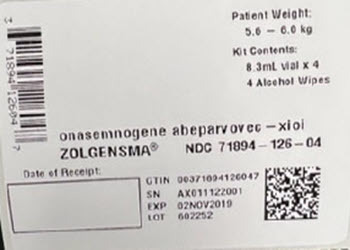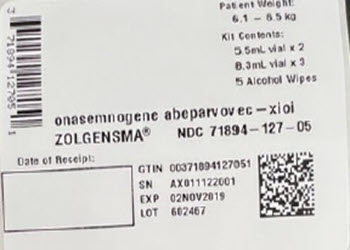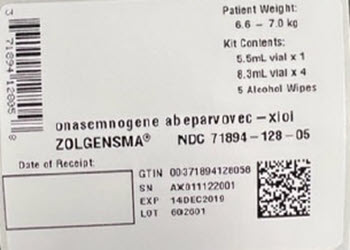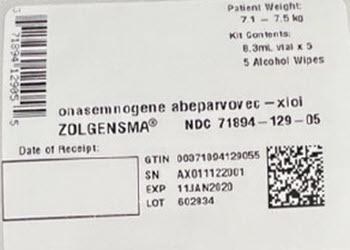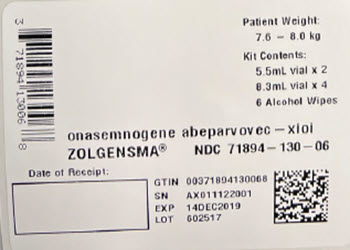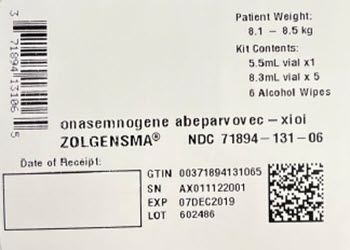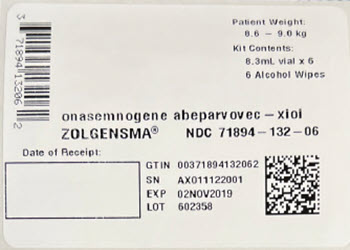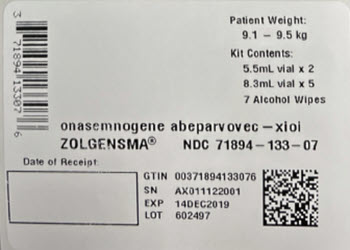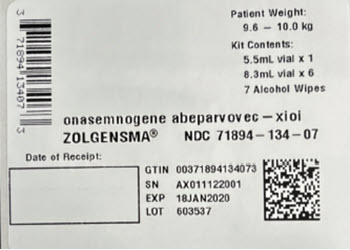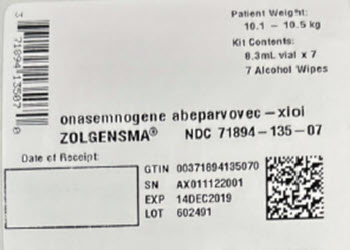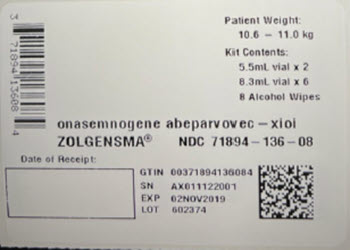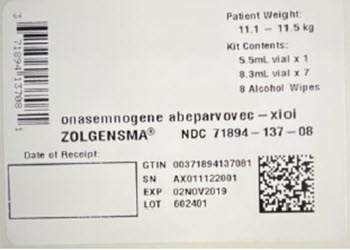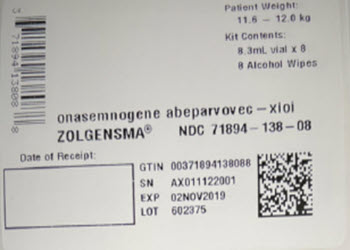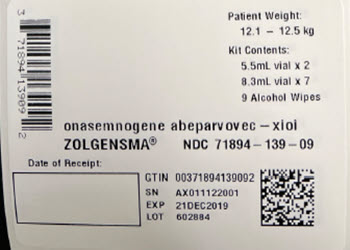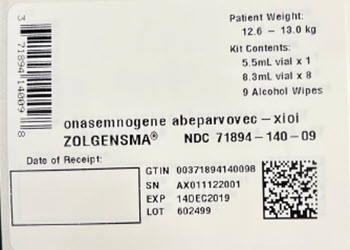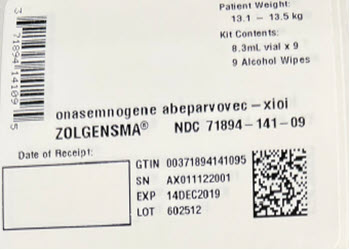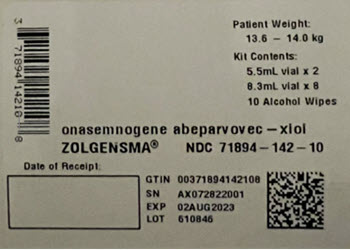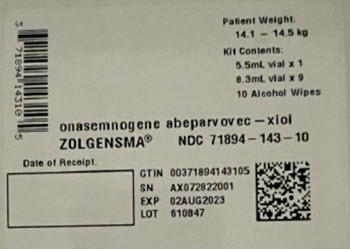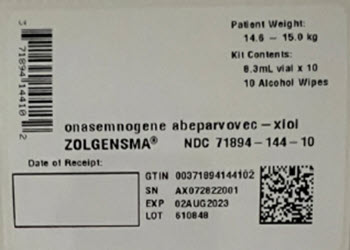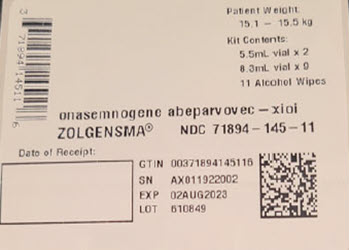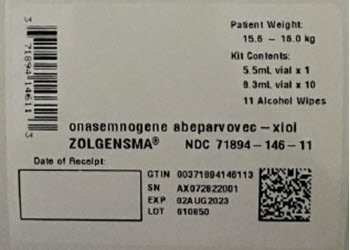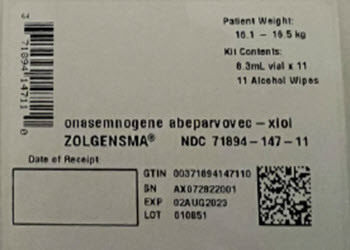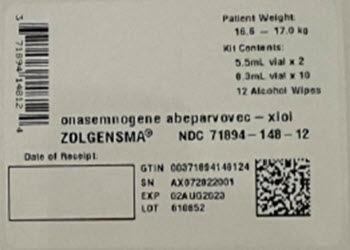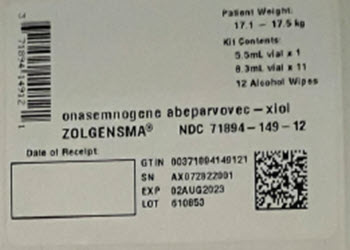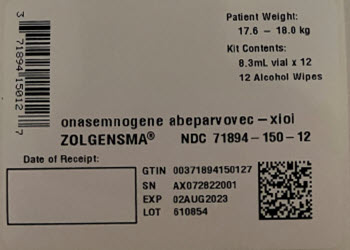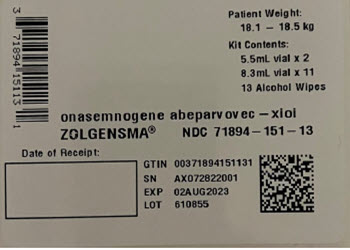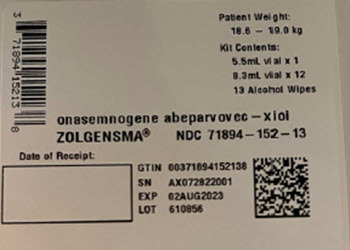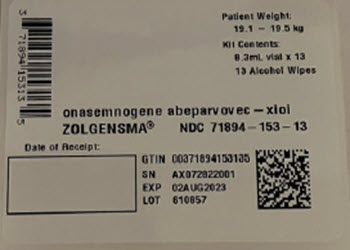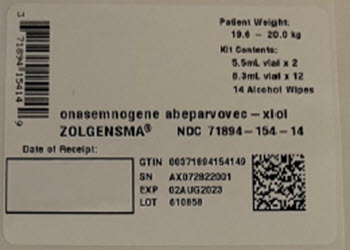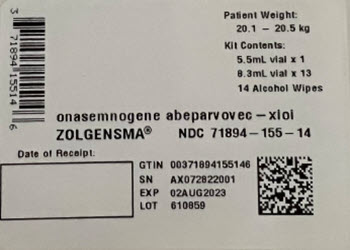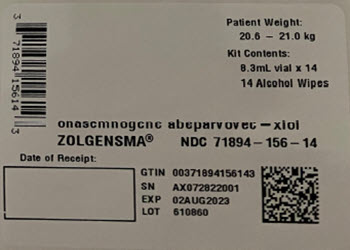 DRUG LABEL: Zolgensma
NDC: 71894-120 | Form: KIT | Route: INTRAVENOUS
Manufacturer: Novartis Gene Therapies, Inc.
Category: prescription | Type: HUMAN PRESCRIPTION DRUG LABEL
Date: 20251218

ACTIVE INGREDIENTS: ADENO-ASSOCIATED VIRUS 20000000000000 [arb'U]/1 mL; ISOPROPYL ALCOHOL 0.7 mL/1 mL
INACTIVE INGREDIENTS: TROMETHAMINE; MAGNESIUM CHLORIDE; SODIUM CHLORIDE; POLOXAMER 188; WATER; WATER

HIGHLIGHTS OF PRESCRIBING INFORMATION

These highlights do not include all the information needed to use ZOLGENSMA safely and effectively. See full prescribing information for ZOLGENSMA.
ZOLGENSMA® (onasemnogene abeparvovec-xioi) suspension, for intravenous infusion
Initial U.S. Approval: 2019

RECENT MAJOR CHANGES

Dosage and Administration (2.1, 2.3) | 2/2025
Warnings and Precautions (5.6) | 10/2024
Warnings and Precautions (5.5, 5.7) | 2/2025

WARNING: SERIOUS LIVER INJURY and ACUTE LIVER FAILURE

See full prescribing information for complete boxed warning.

- Cases of acute liver failure with fatal outcomes have been reported. Acute serious liver injury and elevated aminotransferases can also occur with ZOLGENSMA. (5.1)
- Patients with preexisting liver impairment may be at higher risk. (5.1)
- Prior to infusion, assess liver function of all patients by clinical examination and laboratory testing. Administer systemic corticosteroid to all patients before and after ZOLGENSMA infusion. Continue to monitor liver function for at least 3 months after infusion, and at other times as clinically indicated. (2.1, 2.3)

1 INDICATIONS AND USAGE

ZOLGENSMA is an adeno-associated virus (AAV) vector-based gene therapy indicated for the treatment of pediatric patients less than 2 years of age with spinal muscular atrophy (SMA) with bi-allelic mutations in the survival motor neuron 1 (SMN1) gene. (1)

Limitations of Use

- The safety and effectiveness of repeat administration of ZOLGENSMA have not been evaluated. (1, 6.2)
- The use of ZOLGENSMA in patients with advanced SMA (e.g., complete paralysis of limbs, permanent ventilator dependence) has not been evaluated. (1, 14)

2 DOSAGE AND ADMINISTRATION

For single-dose intravenous infusion only (2).

- The recommended dosage of ZOLGENSMA is 1.1 × 10^14 vector genomes (vg) per kg of body weight. (2.1)
- Administer ZOLGENSMA as an intravenous infusion over 60 minutes. (2.1, 2.3)
- Postpone ZOLGENSMA in patients with infections until the infection has resolved and the patient is clinically stable. (2.1, 5.2)
- Starting one day prior to ZOLGENSMA infusion, administer systemic corticosteroids equivalent to oral prednisolone at 1 mg/kg of body weight per day for a total of 30 days. At the end of the 30-day period, check liver function by clinical examination and by laboratory testing. For patients with unremarkable findings, taper the corticosteroid dose gradually over the next 28 days. If liver function abnormalities persist, continue systemic corticosteroids (equivalent to oral prednisolone at 1 mg/kg/day) until findings become unremarkable, and then taper the corticosteroid dose gradually over the next 28 days or longer if needed. Do not stop systemic corticosteroids abruptly. (2.1)
- If liver function abnormalities continue to persist ≥ 2 × ULN after the 30-day period of systemic corticosteroids, promptly consult a pediatric gastroenterologist or hepatologist. (2.1)

3 DOSAGE FORMS AND STRENGTHS

ZOLGENSMA is a suspension for intravenous infusion, supplied as single-use vials. (3)

ZOLGENSMA is provided in a kit containing 2 to 14 vials, as a combination of 2 vial fill volumes (either 5.5 mL or 8.3 mL). All vials have a nominal concentration of 2.0 × 10^13 vector genomes (vg) per mL. Each vial of ZOLGENSMA contains an extractable volume of not less than either 5.5 mL or 8.3 mL. (3)

4 CONTRAINDICATIONS

None. (4)

5 WARNINGS AND PRECAUTIONS

- Systemic Immune Response: Administer ZOLGENSMA to patients who are clinically stable in their overall baseline health status (e.g., hydration and nutritional status, absence of infection) prior to infusion. (5.2)
- Thrombocytopenia: Monitor platelet counts before ZOLGENSMA infusion, and at least weekly for the first month and then every other week for the second and third month or until platelet counts return to baseline. (2.3, 5.3)
- Thrombotic Microangiopathy (TMA): Prompt attention to signs and symptoms of TMA is advised, as TMA can result in life-threatening or fatal outcomes. If clinical signs, symptoms and/or laboratory findings occur, consult a pediatric hematologist and/or pediatric nephrologist immediately to manage as clinically indicated. (5.4)
- Elevated Troponin I: Increases in cardiac troponin I levels have occurred following ZOLGENSMA infusion. Consider cardiac evaluation after ZOLGENSMA infusion and consult a cardiologist as needed. (5.5)
- AAV Vector Integration and Risk of Tumorigenicity: There is a theoretical risk of tumorigenicity due to integration of AAV vector DNA into the genome. Report cases of tumors in patients who received ZOLGENSMA, to Novartis Gene Therapies, Inc. (5.6, 17)
- Infusion-Related Reactions: Monitor patients during and after ZOLGENSMA infusion. Interrupt ZOLGENSMA infusion if infusion-related reaction occurs and administer supportive treatment as appropriate. Infusion of ZOLGENSMA may be resumed based on clinical assessment. (5.7)

6 ADVERSE REACTIONS

The most common adverse reactions (incidence ≥ 5%) were elevated aminotransferases and vomiting. (6)

To report SUSPECTED ADVERSE REACTIONS, contact Novartis Gene Therapies at 1-833-828-3947 or FDA at 1-800-FDA-1088 or www.fda.gov/medwatch.

7 DRUG INTERACTIONS

Where feasible, adjust a patient’s vaccination schedule to accommodate concomitant corticosteroid administration prior to and following ZOLGENSMA infusion. (7)

8 USE IN SPECIFIC POPULATIONS

Pediatric Use: Use of ZOLGENSMA in premature neonates before reaching full term gestational age is not recommended because concomitant treatment with corticosteroids may adversely affect neurological development. Delay ZOLGENSMA infusion until full-term gestational age is reached. (8.4)

FULL PRESCRIBING INFORMATION

WARNING: SERIOUS LIVER INJURY and ACUTE LIVER FAILURE

- Cases of acute liver failure with fatal outcomes have been reported. Acute serious liver injury and elevated aminotransferases can also occur with ZOLGENSMA [see Warnings and Precautions (5.1)].
- Patients with preexisting liver impairment may be at higher risk [see Warnings and Precautions (5.1)].
- Prior to infusion, assess liver function of all patients by clinical examination and laboratory testing. Administer systemic corticosteroid to all patients before and after ZOLGENSMA infusion. Continue to monitor liver function for at least 3 months after infusion, and at other times as clinically indicated [see Dosage and Administration (2.1, 2.3)].

1 INDICATIONS AND USAGE

ZOLGENSMA is an adeno-associated virus (AAV) vector-based gene therapy indicated for the treatment of pediatric patients less than 2 years of age with spinal muscular atrophy (SMA) with bi-allelic mutations in the survival motor neuron 1 (SMN1) gene.

Limitations of Use

- The safety and effectiveness of repeat administration of ZOLGENSMA have not been evaluated [see Adverse Reactions (6.2)].
- The use of ZOLGENSMA in patients with advanced SMA (e.g., complete paralysis of limbs, permanent ventilator-dependence) has not been evaluated [see Clinical Studies (14)].

2 DOSAGE AND ADMINISTRATION

For single-dose intravenous infusion only.

2.1 Dose and Administration

The recommended dose of ZOLGENSMA is 1.1 × 10^14 vector genomes per kilogram (vg/kg) of body weight.

Table 1: Dosing
Patient weight range (kg) | Dose volumea (mL)
2.6 – 3.0 | 16.5
3.1 – 3.5 | 19.3
3.6 – 4.0 | 22.0
4.1 – 4.5 | 24.8
4.6 – 5.0 | 27.5
5.1 – 5.5 | 30.3
5.6 – 6.0 | 33.0
6.1 – 6.5 | 35.8
6.6 – 7.0 | 38.5
7.1 – 7.5 | 41.3
7.6 – 8.0 | 44.0
8.1 – 8.5 | 46.8
8.6 – 9.0 | 49.5
9.1 – 9.5 | 52.3
9.6 – 10.0 | 55.0
10.1 – 10.5 | 57.8
10.6 – 11.0 | 60.5
11.1 – 11.5 | 63.3
11.6 – 12.0 | 66.0
12.1 – 12.5 | 68.8
12.6 – 13.0 | 71.5
13.1 – 13.5 | 74.3
13.6 – 14.0 | 77.0
14.1 – 14.5 | 79.8
14.6 – 15.0 | 82.5
15.1 – 15.5 | 85.3
15.6 – 16.0 | 88.0
16.1 – 16.5 | 90.8
16.6 – 17.0 | 93.5
17.1 – 17.5 | 96.3
17.6 – 18.0 | 99.0
18.1 – 18.5 | 101.8
18.6 – 19.0 | 104.5
19.1 – 19.5 | 107.3
19.6 – 20.0 | 110.0
20.1 – 20.5 | 112.8
20.6 – 21.0 | 115.5
aDose volume is calculated using the upper limit of the patient weight range for pediatric patients less than 2 years of age between 2.6 kg and 21.0 kg.

- Prior to ZOLGENSMA infusion:
  - Due to the increased risk of serious systemic immune response, administer ZOLGENSMA to patients who are clinically stable in their overall baseline health status (e.g., hydration and nutritional status, absence of infection) prior to infusion. Postpone ZOLGENSMA in patients with infections until the infection has resolved and the patient is clinically stable. Clinical signs or symptoms of infection should not be evident at the time of ZOLGENSMA infusion [see Warnings and Precautions (5.2, 5.4), Patient Counseling Information (17)].
  - Assess liver function [see Boxed Warning, Dosage and Administration (2.3), Warnings and Precautions (5.1), Use in Specific Populations (8.6)].
  - Obtain creatinine and complete blood count (including hemoglobin and platelet count) [see Dosage and Administration (2.3), Warnings and Precautions (5.3, 5.4)].
  - Perform baseline testing for the presence of anti-AAV9 antibodies [see Dosage and Administration (2.3), Adverse Reactions (6.2)].
- One day prior to ZOLGENSMA infusion, begin administration of systemic corticosteroids equivalent to oral prednisolone at 1 mg per kg of body weight per day (mg/kg/day) for a total of 30 days.
- Administer ZOLGENSMA as a single-dose intravenous infusion through a venous catheter.

Follow the steps below for infusion:

1. Place a primary catheter into a vein (generally a peripheral vein in the arm or leg). Insertion of a back-up catheter is recommended.
2. Program syringe pump for saline priming, or prime tubing manually with saline.
3. Administer ZOLGENSMA as a slow infusion over 60 minutes. DO NOT INFUSE AS AN INTRAVENOUS PUSH OR BOLUS.
4. Flush line with saline following completion of infusion.

- Monitor liver function by clinical examination and by laboratory testing on a regular basis, and at other times as clinically indicated [see Dosage and Administration (2.3)].

- At the end of the 30-day period of systemic corticosteroid treatment, check liver status clinically and by assessing alanine aminotransferase (ALT), aspartate aminotransferase (AST), total bilirubin, prothrombin time, and international normalized ratio (INR).
- Promptly assess and closely monitor patients with worsening liver function test results and/or signs or symptoms of acute illness (e.g., vomiting, deterioration in health) [see Warnings and Precautions (5.1)].
- For patients with unremarkable findings (normal clinical exam, total bilirubin, prothrombin time, and INR and ALT and AST levels below 2 × upper limit of normal [ULN]): Taper the corticosteroid dose gradually over the next 28 days. Do not stop systemic corticosteroids abruptly [see Warnings and Precautions (5.1)].
- If liver function abnormalities persist, continue systemic corticosteroids (equivalent to oral prednisolone at 1 mg/kg/day) until AST and ALT values are both below 2 × ULN and all other assessments return to normal range, and then taper the corticosteroid dose gradually over the next 28 days or longer if needed. Do not stop systemic corticosteroids abruptly [see Warnings and Precautions (5.1)].
- If liver function abnormalities continue to persist ≥ 2 × ULN after the 30-day period of systemic corticosteroids, promptly consult a pediatric gastroenterologist or hepatologist [see Warnings and Precautions (5.1)].
- If oral corticosteroid therapy is not tolerated, consider intravenous corticosteroids as clinically indicated [see Warnings and Precautions (5.1)].

2.2 Preparation

- Thaw ZOLGENSMA before use. The contents of the ZOLGENSMA kit will thaw in approximately 16 hours if placed in a refrigerator, or in approximately 6 hours if placed at room temperature. If thawed in a refrigerator, remove from refrigerator on day of dosing.
- When thawed, ZOLGENSMA is a clear to slightly opaque, colorless to faint white liquid, free of particles. Visually inspect vials for particulate matter and discoloration prior to infusion. Do not use vials if particulates or discoloration are present.
- DO NOT SHAKE.
- Draw the appropriate dose volume from all vials into a syringe, remove air from the syringe, cap the syringe, and deliver the syringe at room temperature to the patient infusion location.
- Use ZOLGENSMA within 8 hours of drawing into syringe. Discard the vector-containing syringe if the drug is not infused within the 8-hour timeframe.
- DO NOT REFREEZE.

2.3 Laboratory Testing and Monitoring to Assess Safety

Perform baseline anti-AAV9 antibody testing prior to ZOLGENSMA infusion. Retesting may be performed if anti-AAV9 antibody titers are reported as > 1:50 [see Dosage and Administration (2.1)].

Conduct the following tests at baseline and as directed below [see Warnings and Precautions (5.1, 5.3, 5.5)]:

- Liver function (clinical exam, AST, ALT, total bilirubin, albumin, prothrombin time, partial thromboplastin time [PTT], and INR) at baseline. Monitor liver function (AST, ALT, total bilirubin, prothrombin time, INR) weekly for the first month after ZOLGENSMA infusion and during the corticosteroid taper period (28 days or longer if needed). If the patient is clinically stable with unremarkable findings (normal clinical exam, total bilirubin, and prothrombin and INR results, and ALT and AST levels below 2 × ULN) at the end of the corticosteroid taper period, continue to monitor liver function every other week for another month.
- Platelet counts weekly for the first month, and then every other week for the second and third months, until platelet counts return to baseline.

3 DOSAGE FORMS AND STRENGTHS

ZOLGENSMA is a suspension for intravenous infusion.

ZOLGENSMA is provided in a kit containing 2 to 14 vials. Vials are provided in 2 fill volumes: 5.5 mL or 8.3 mL.

ZOLGENSMA has a nominal concentration of 2.0 × 10^13 vg/mL, and each vial contains an extractable volume of not less than either 5.5 mL or 8.3 mL.

The intravenous dosage is determined by patient body weight, with a recommended dose of 1.1 × 10^14 vg/kg for pediatric patients.

4 CONTRAINDICATIONS

None.

5 WARNINGS AND PRECAUTIONS

5.1 Acute Serious Liver Injury, Acute Liver Failure or Elevated Aminotransferases

Acute serious liver injury, acute liver failure and elevated aminotransferases can occur with ZOLGENSMA. Hepatotoxicity (which may be immune-mediated), generally manifested as elevated ALT and/or AST levels. Acute serious liver injury and acute liver failure, including fatal cases, have been reported with ZOLGENSMA use [see Adverse Reactions (6)]. In order to mitigate potential aminotransferase elevations, administer systemic corticosteroid to all patients before and after ZOLGENSMA infusion. Immune-mediated hepatotoxicity may require adjustment of the corticosteroid treatment regimen, including longer duration, increased dose, or prolongation of the corticosteroid taper [see Dosage and Administration (2.1)].

Patients with preexisting liver impairment or acute hepatic viral infection may be at higher risk of acute serious liver injury/acute liver failure. Patients with ALT, AST, or total bilirubin levels (except due to neonatal jaundice) > 2 × ULN have not been studied in clinical trials with ZOLGENSMA. Carefully consider the risks and benefits of ZOLGENSMA therapy in patients with preexisting liver impairment.

Although in the clinical trials and in postmarketing experience, asymptomatic aminotransferase elevations were very commonly reported [see Adverse Reactions (6.1)], in the managed access program and in the postmarketing setting, cases of acute serious liver injury and acute liver failure, including a few cases with fatal outcomes, have been reported. Some patients have experienced elevations in ALT and AST > 20 × ULN, prolonged prothrombin time and have been symptomatic (e.g., vomiting, jaundice), which required the use of corticosteroids, sometimes with prolonged duration and/or a higher dose. If acute serious liver injury or acute liver failure is suspected, promptly consult a pediatric gastroenterologist or hepatologist.

Prior to ZOLGENSMA infusion, assess liver function by clinical examination and laboratory testing (hepatic aminotransferases [AST and ALT], total bilirubin level, albumin, prothrombin time, PTT, and INR). Continue to monitor liver function (AST, ALT, total bilirubin, prothrombin time, INR) for at least 3 months after ZOLGENSMA infusion, and at other times as clinically indicated.

Promptly assess and closely monitor patients with worsening liver function test results and/or signs or symptoms of acute illness (e.g., vomiting, deterioration in health). In case hepatic injury is suspected, further testing of albumin, PTT, and INR is recommended.

Monitor liver function weekly for the first month after ZOLGENSMA infusion and during the corticosteroid taper period (28 days or longer if needed). If the patient is clinically stable with unremarkable findings at the end of the corticosteroid taper period, continue to monitor liver function every other week for another month [see Dosage and Administration (2.3)].

5.2 Systemic Immune Response

Due to activation of humoral and cellular immunity following ZOLGENSMA infusion, patients with underlying active infection, either acute (e.g., respiratory, gastrointestinal) or chronic uncontrolled (e.g., chronic active hepatitis B), could be at an increased risk of serious systemic immune response, potentially resulting in more severe clinical courses of the infection. Serious systemic immune response can present with a variety of findings (e.g., high fever, hypotension, etc.). Patients with infection were excluded from participation in ZOLGENSMA clinical trials. Recommend increased vigilance in the prevention, monitoring, and management of infection before and after ZOLGENSMA infusion.

To mitigate the risk of serious and life-threatening systemic immune response, administer ZOLGENSMA to patients who are clinically stable in their overall baseline health status (e.g., hydration and nutritional status, absence of infection) prior to infusion. Postpone ZOLGENSMA in patients with infections until the infection has resolved and the patient is clinically stable. Clinical signs or symptoms of infection should not be evident at the time of ZOLGENSMA infusion [see Dosage and Administration (2.1)]. Recommend seasonal prophylaxis against influenza and respiratory syncytial virus (RSV) and vaccination status should be up-to-date prior to ZOLGENSMA administration.

5.3 Thrombocytopenia

Transient decreases in platelet counts, some of which met the criteria for thrombocytopenia, were typically observed within the first two weeks after ZOLGENSMA infusion.

Monitor platelet counts before ZOLGENSMA infusion and closely monitor platelet counts within the first two weeks following infusion and on a regular basis afterwards (at least weekly for the first month; every other week for the second and third months or until platelet counts return to baseline) [see Dosage and Administration (2.3)].

5.4 Thrombotic Microangiopathy

Cases of thrombotic microangiopathy (TMA) were reported to occur generally within the first two weeks after ZOLGENSMA infusion in the post-marketing setting [see Adverse Reactions (6.3)]. TMA is characterized by thrombocytopenia, microangiopathic hemolytic anemia, and acute kidney injury. Concurrent immune system activation (e.g., infections, vaccinations) was identified in some cases.

Prompt attention to signs and symptoms of TMA is advised, as TMA can result in life-threatening or fatal outcomes.

Monitor platelet counts closely within the first two weeks following infusion and on a regular basis afterwards [see Warnings and Precautions (5.3)], as well as signs and symptoms of TMA, such as hypertension, increased bruising, seizures, or decreased urine output. In case these signs and symptoms occur in the presence of thrombocytopenia, further diagnostic evaluation for hemolytic anemia and renal dysfunction should be promptly undertaken. If clinical signs, symptoms and/or laboratory findings consistent with TMA occur, consult a pediatric hematologist and/or pediatric nephrologist immediately to manage TMA as clinically indicated.

5.5 Elevated Troponin I

Increases in cardiac troponin I levels (up to 0.176 mcg/L) have occurred following ZOLGENSMA infusion in clinical trials. Cardiac toxicity was observed in animal studies [see Nonclinical Toxicology (13.2)]. Consider cardiac evaluation after ZOLGENSMA infusion and consult a cardiologist as needed.

5.6 AAV Vector Integration and Risk of Tumorigenicity

There is a theoretical risk of tumorigenicity due to integration of AAV vector DNA into the genome.

ZOLGENSMA is composed of a recombinant, non-replicating AAV9 vector whose DNA persists largely in episomal form. Random integration of recombinant AAV vector DNA into human DNA has been reported with ZOLGENSMA and in published literature about other AAV gene therapies. The clinical relevance of individual integration events is unknown, but it is acknowledged that individual integration events could potentially contribute to a risk of tumorigenicity. Cases of tumor have been reported in patients who received ZOLGENSMA post-approval. A causal relationship with ZOLGENSMA has not been established based on tumor analyses. However, in some cases, limited information was available. If a tumor develops in a patient receiving ZOLGENSMA, healthcare providers should contact and report the tumor to Novartis Gene Therapies, Inc. at 1-833-828-3947.

5.7 Infusion-Related Reactions

Infusion-related reactions, including hypersensitivity reactions and anaphylaxis, have occurred with ZOLGENSMA infusion [see Adverse Reactions (6.3)]. Signs and symptoms may include rash, urticaria, vomiting, dyspnea, respiratory symptoms and/or alterations in heart rate and blood pressure. Monitor patients during and after treatment with ZOLGENSMA. If an infusion-related reaction occurs, interrupt ZOLGENSMA infusion and administer supportive treatment to manage the infusion-related reaction as appropriate. Infusion of ZOLGENSMA may be resumed based on clinical assessment.

6 ADVERSE REACTIONS

The most common adverse reactions (incidence ≥ 5%) were elevated aminotransferases and vomiting.

6.1 Clinical Trials Experience

Because clinical trials are conducted under widely varying conditions, adverse reaction rates observed in the clinical trials of a drug cannot be directly compared to rates in the clinical trials of another product and may not reflect the rates observed in practice.

The safety data described in this section reflect exposure to ZOLGENSMA in five clinical studies enrolling a total of 68 patients. This includes four prospective open-label clinical trials [NCT03306277 (Study 1), NCT02122952 (Study 2), NCT03505099, NCT04851873 (Study 3)], and one observational long-term follow-up study [NCT03421977]. The patient population in NCT03306277, NCT03505099, and NCT02122952 ranged in age from 0.3 months to 7.9 months at the time of infusion (median age, 3.3 months), with weight range from 3.0 kg to 8.4 kg (median weight, 5.5 kg) [see Clinical Studies (14)].

In an open-label, post-authorization clinical study (Study 3, NCT04851873), safety of ZOLGENSMA was evaluated in 24 children, aged between 1.5 to 9.1 years (median age, 4.9 years), with weight range from ≥ 8.5 kg to ≤ 21 kg (median weight, 15.8 kg). Only one of the 24 patients was under the age of 2 years at the time of ZOLGENSMA administration. Patients in Study 3 had 2 to 4 copies of SMN2. Before treatment with ZOLGENSMA, 21 patients discontinued their previous treatment with nusinersen or risdiplam. The types of adverse reactions observed in Study 3 were consistent with those of Studies 1 and 2. Liver enzyme increases in Study 3 occurred at a higher frequency compared with the previous 4 studies. AST or ALT elevations > 2 × ULN were observed in the majority of patients (23 out of 24 patients), including 21 patients with ALT elevations > 3 × ULN and 5 patients with ALT elevations > 20 × ULN. These patients were clinically asymptomatic and there were no elevations of bilirubin. The AST and ALT elevations were managed with the use of corticosteroids, typically with prolonged duration and/or given at a higher dose [see Warnings and Precautions (5.1)]. Transient decreases in platelet counts, which met the criteria for thrombocytopenia were observed in 20 out of 24 patients. Four patients had platelet counts below 50,000 per µL [see Warnings and Precautions (5.3)].

The most frequent adverse reactions (incidence ≥ 5%) and increases in alanine aminotransferase in the 4 studies (data cut-off date: September 27, 2018) are summarized in Table 2.

Table 2: Adverse Reactions and ALT Increases* Following Treatment With ZOLGENSMA
 | Patients n = 44 (3.0-8.4 kg)
Adverse reactions | n (%)
Elevated aminotransferases | 12 (27%)
ALT > 3 X ULN | 7 (16%)
ALT > 20 X ULN | 4 (9%)
Vomiting | 3 (7%)
Abbreviations: ULN, upper limit of normal; ALT, alanine aminotransferase.
*Laboratory finding.

One death occurred in a patient, who received ZOLGENSMA at the age of 5 months (6 kg), in a completed non-United States clinical trial (NCT03461289). The patient initially presented with respiratory insufficiency 12 days after ZOLGENSMA infusion and was found to have RSV and parainfluenza in respiratory secretions. The patient had episodes of serious hypotension, followed by seizures, and was found to have leukoencephalopathy (brain white matter defects) approximately 30 days after ZOLGENSMA infusion. The patient died after withdrawal of life support 52 days after ZOLGENSMA infusion.

6.2 Immunogenicity

In ZOLGENSMA clinical trials, patients were required to have baseline anti-AAV9 antibody titers of ≤ 1:50, measured using an enzyme-linked immunosorbent assay (ELISA). Evidence of prior exposure to AAV9 was uncommon. The safety and efficacy of ZOLGENSMA in patients with anti-AAV9 antibody titers above 1:50 have not been evaluated. Perform baseline testing for the presence of anti-AAV9 antibodies prior to ZOLGENSMA infusion. Retesting may be performed if anti-AAV9 antibody titers are reported as > 1:50 [see Dosage and Administration (2.1, 2.3)].

Following ZOLGENSMA infusion, increases from baseline in anti-AAV9 antibody titers occurred in all patients. In Study 2, anti-AAV9 antibody titers reached at least 1:102,400 in every patient, and titers exceeded 1:819,200 in most patients. Re-administration of ZOLGENSMA in the presence of high anti-AAV9 antibody titer has not been evaluated.

6.3 Postmarketing Experience

The following adverse reactions have been identified during post-approval use of ZOLGENSMA. Because these reactions are reported voluntarily, it is not always possible to reliably estimate their frequency or establish a causal relationship to drug exposure.

Blood and Lymphatic System Disorders: thrombotic microangiopathy [see Warnings and Precautions (5.4)], thrombocytopenia [see Warnings and Precautions (5.3)]

Hepatobiliary Disorders: acute liver failure (fatal and non-fatal), acute liver injury [see Warnings and Precautions (5.1)]

General Disorders and Administration Site Conditions: pyrexia, infusion-related reactions [see Warnings and Precautions (5.7)]

Investigations: troponin increased [see Warnings and Precautions (5.5)]

7 DRUG INTERACTIONS

Where feasible, adjust a patient’s vaccination schedule to accommodate concomitant corticosteroid administration prior to and following ZOLGENSMA infusion [see Dosage and Administration (2.1)]. Certain vaccines, such as measles, mumps, and rubella (MMR) and varicella, are contraindicated for patients on a substantially immunosuppressive steroid dose (i.e., ≥ 2 weeks of daily receipt of 20 mg or 2 mg/kg body weight of prednisone or equivalent). Seasonal RSV prophylaxis is recommended (General Best Practice Guidelines for Immunization [www.cdc.gov/vaccines/hcp/acip-recs/general-recs/downloads/general-recs.pdf], eds2017).

8 USE IN SPECIFIC POPULATIONS

8.1 Pregnancy

Risk Summary

There are no available data regarding ZOLGENSMA use in pregnant women. No animal reproductive and developmental toxicity studies have been conducted with ZOLGENSMA.

In the United States general population, the estimated background risk of major birth defects and miscarriage in clinically recognized pregnancies is 2% to 4% and 15% to 20%, respectively.

8.2 Lactation

Risk Summary

There is no information available on the presence of ZOLGENSMA in human milk, the effects on the breastfed infant, or the effects on milk production. The developmental and health benefits of breastfeeding should be considered along with the mother’s clinical need for ZOLGENSMA and any potential adverse effects on the breastfed child from ZOLGENSMA or from the underlying maternal condition.

There is no information on whether breastfeeding should be restricted in mothers who may be seropositive for anti-AAV9 antibodies.

8.4 Pediatric Use

The safety of ZOLGENSMA was studied in pediatric patients who received ZOLGENSMA infusion at age 0.3 to 7.9 months (weight range, 3.0 kg to 8.4 kg). Safety was also studied in Study 3 (post-authorization study) in patients weighing 9.5 kg to 20.2 kg [see Adverse Reactions (6)].

The efficacy of ZOLGENSMA was studied in pediatric patients who received ZOLGENSMA infusion at age 0.5 to 7.9 months (weight range, 3.6 kg to 8.4 kg) [see Clinical Studies (14)].

Administration of ZOLGENSMA to premature neonates before reaching full-term gestational age is not recommended, because concomitant treatment with corticosteroids may adversely affect neurological development. Delay ZOLGENSMA infusion until the corresponding full-term gestational age is reached.

8.6 Hepatic Impairment

ZOLGENSMA therapy should be carefully considered in patients with liver impairment. Cases of acute serious liver injury and acute liver failure have been reported with ZOLGENSMA in patients with preexisting liver abnormalities. In clinical trials, elevation of aminotransferases was observed in patients following ZOLGENSMA infusion [see Warnings and Precautions (5.1)].

11 DESCRIPTION

ZOLGENSMA is a suspension of an adeno-associated viral vector-based gene therapy for intravenous infusion. It is a recombinant self-complementary AAV9 containing a transgene encoding the human survival motor neuron (SMN) protein, under the control of a cytomegalovirus enhancer/chicken-β-actin hybrid promoter.

ZOLGENSMA has a nominal concentration of 2.0 × 10^13 vg/mL. Each vial contains an extractable volume of not less than either 5.5 mL or 8.3 mL and the excipients 20 mM Tris (pH 8.0), 1 mM magnesium chloride (MgCl2), 200 mM sodium chloride (NaCl) and 0.005% poloxamer 188. ZOLGENSMA is packaged as a sterile suspension and contains no preservative.

12 CLINICAL PHARMACOLOGY

12.1 Mechanism of Action

Onasemnogene abeparvovec is a recombinant AAV9-based gene therapy designed to deliver a copy of the gene encoding the human SMN protein. SMA is caused by a bi-allelic mutation in the SMN1 gene, which results in insufficient SMN protein expression. Intravenous administration of ZOLGENSMA that results in cell transduction and expression of the SMN protein has been observed in two human case studies [see Clinical Pharmacology (12.3)].

12.2 Pharmacodynamics

There are no clinically relevant pharmacodynamics data for onasemnogene abeparvovec.

12.3 Pharmacokinetics

Vector shedding after infusion with onasemnogene abeparvovec was investigated at multiple time points during Study 2. Samples of saliva, urine and stool were collected the day after infusion, weekly through Day 30, and then monthly through Month 12 and every 3 months thereafter. Samples from 5 patients were used for onasemnogene abeparvovec vector DNA shedding analysis through the Month 18 visit.

Vector DNA was shed in saliva, urine and stool after infusion of onasemnogene abeparvovec, with much higher concentrations of vector DNA found in stool than in saliva or urine. The vector DNA concentration in saliva was low on Day 1 after infusion and declined to undetectable levels within 3 weeks. In urine, the vector DNA concentration was very low on Day 1 after infusion and declined to undetectable levels within 1 to 2 weeks. In stool, the vector DNA concentration was much higher than in saliva or urine for 1 to 2 weeks after infusion and declined to undetectable levels by 1 to 2 months after infusion.

Biodistribution was evaluated in two patients who died 5.7 months and 1.7 months, respectively, after infusion of onasemnogene abeparvovec at the dose of 1.1 x 10^14 vg/kg. Both cases showed that the highest levels of vector DNA were found in the liver. Vector DNA was also detected in the spleen, heart, pancreas, inguinal lymph node, skeletal muscles, peripheral nerves, kidney, lung, intestines, gonads, spinal cord, brain, and thymus. Immunostaining for SMN protein showed generalized SMN expression in spinal motor neurons, neuronal and glial cells of the brain, and in the heart, liver, skeletal muscles, and other tissues evaluated.

13 NONCLINICAL TOXICOLOGY

13.1 Carcinogenesis, Mutagenesis, Impairment of Fertility

No animal studies have been performed to evaluate the effects of onasemnogene abeparvovec on carcinogenesis, mutagenesis, or impairment of fertility.

13.2 Animal Toxicology and/or Pharmacology

In toxicology studies conducted in neonatal mice, dose-dependent cardiac and hepatic toxicities were observed following intravenous administration of onasemnogene abeparvovec. Onasemnogene abeparvovec-related findings in the myocardium, at doses of 7.9 × 10^13 vg/kg and higher, included slight to mild mononuclear cell inflammation accompanied by edema, slight to mild fibrosis, and scattered myocardial cell degeneration/regeneration. Additional cardiac findings at dose levels of 1.5 × 10^14 vg/kg and higher included minimal to moderate atrial thrombosis and slight to marked atrial dilation. Liver findings included hepatocellular hypertrophy, Kupffer cell activation, perinuclear vacuolation, and scattered hepatocellular necrosis. Target organ toxicity in the heart and liver was associated with mortality in mice at dose levels of 2.4 × 10^14 vg/kg and above, approximately 2.2-fold higher than the recommended clinical dose level.

In a 6-month toxicology study conducted in juvenile non-human primates, single intravenous administration of onasemnogene abeparvovec at the recommended clinical dose level of 1.1 × 10^14 vg/kg, with or without corticosteroid treatment, resulted in microscopic findings in the dorsal root ganglia (DRG), trigeminal ganglia (TG), spinal cord, brainstem, and liver. At 6 weeks post-administration, microscopic findings included minimal to slight mononuclear cell inflammation and neuronal degeneration in the DRG and TG; axonal degeneration and gliosis in the spinal cord; mixed cell inflammation, gliosis, and axonal degeneration in the brainstem; and oval cell hyperplasia in the liver. These microscopic findings were still present at 6 months with decreased severity and incidence.

14 CLINICAL STUDIES

The efficacy of ZOLGENSMA in pediatric patients less than 2 years of age with SMA with bi-allelic mutations in the SMN1 gene was evaluated in an open-label, single-arm clinical trial (Study 1, NCT03306277) and an open-label, single-arm, ascending-dose clinical trial (Study 2, NCT02122952). Patients experienced onset of clinical symptoms consistent with SMA before 6 months of age. All patients had genetically confirmed bi-allelic SMN1 gene deletions, 2 copies of the SMN2 gene, and absence of the c.859G>C modification in exon 7 of SMN2 gene (which predicts a milder phenotype). All patients had baseline anti-AAV9 antibody titers of ≤ 1:50, measured by ELISA. In both trials, ZOLGENSMA was delivered as a single-dose intravenous infusion.

Efficacy was established on the basis of survival, and achievement of developmental motor milestones, such as sitting without support. Survival was defined as time from birth to either death or permanent ventilation. Permanent ventilation was defined as requiring invasive ventilation (tracheostomy), or respiratory assistance for 16 or more hours per day (including noninvasive ventilatory support) continuously for 14 or more days in the absence of an acute reversible illness, excluding perioperative ventilation. Efficacy was also supported by assessments of ventilator use, nutritional support and scores on the Children's Hospital of Philadelphia Infant Test of Neuromuscular Disorders (CHOP-INTEND). CHOP-INTEND is an assessment of motor skills in patients with infantile-onset SMA.

Study 1 enrolled 21 patients (10 male and 11 female) with infantile-onset SMA. Before treatment with ZOLGENSMA, none of the 21 patients required noninvasive ventilator (NIV) support, and all patients could exclusively feed orally (i.e., no need for non-oral nutrition). The mean CHOP-INTEND score at baseline was 31.0 (range, 18 to 47). All the patients received 1.1 × 10^14 vg/kg of ZOLGENSMA. The mean age of the 21 patients at the time of treatment was 3.9 months (range, 0.5 to 5.9 months).

As of the March 2019 data cutoff, 19 patients were alive without permanent ventilation (i.e., event-free survival) and were continuing in the trial, while one patient died at age 7.8 months due to disease progression, and one patient withdrew from the study at age 11.9 months. The 19 surviving patients who were continuing in the trial ranged in age from 9.4 to 18.5 months. By the data cutoff, 13 of the 19 patients continuing in the trial reached 14 months of age without permanent ventilation, one of the study’s co-primary efficacy endpoints. In addition to survival, assessment of the other co-primary efficacy endpoint found that 10 of the 21 patients (47.6%) achieved the ability to sit without support for ≥ 30 seconds between 9.2 and 16.9 months of age (mean age was 12.1 months). Based on the natural history of the disease, patients who met the study entry criteria would not be expected to attain the ability to sit without support, and only approximately 25% of these patients would be expected to survive (i.e., being alive without permanent ventilation) beyond 14 months of age. In addition, 16 of the 19 patients had not required daily NIV use.

Comparison of the results of Study 1 to available natural history data of patients with infantile-onset SMA provides primary evidence of the effectiveness of ZOLGENSMA.

Study 2 enrolled 15 patients (6 male and 9 female) with infantile-onset SMA, 3 in a low-dose cohort and 12 in a high-dose cohort. At the time of treatment, the mean age of patients in the low-dose cohort was 6.3 months (range, 5.9 to 7.2 months), and 3.4 months (range, 0.9 to 7.9 months) in the high-dose cohort. The dosage received by patients in the low-dose cohort was approximately one-third of the dosage received by patients in the high-dose cohort. However, the precise dosages of ZOLGENSMA received by patients are unclear due to a change in the method of measuring ZOLGENSMA concentration, and to decreases in the concentration of stored ZOLGENSMA over time. The retrospectively-estimated dosage range in the high-dose cohort is approximately 1.1 × 10^14 to 1.4 × 10^14 vg/kg.

By 24 months following ZOLGENSMA infusion, one patient in the low-dose cohort met the endpoint of permanent ventilation; all 12 patients in the high-dose cohort were alive without permanent ventilation. None of the patients in the low-dose cohort were able to sit without support, or to stand or walk; in the high-dose cohort, 9 of the 12 patients (75.0%) were able to sit without support for ≥ 30 seconds, and 2 patients (16.7%) were able to stand and walk without assistance. Comparison of the results of the low-dose cohort to the results of the high-dose cohort shows a dose-response relationship that supports the effectiveness of ZOLGENSMA.

16 HOW SUPPLIED/STORAGE AND HANDLING

16.1 How Supplied

ZOLGENSMA is shipped frozen (≤ -60°C [-76°F]) in 10 mL vials with 2 fill volumes (either 5.5 mL or 8.3 mL).

ZOLGENSMA is provided as a customized kit to meet dosing requirements for each patient [see Dosage and Administration (2.1)], with each kit containing:

- Two (2) to fourteen (14) vials of ZOLGENSMA (see below)
- One alcohol wipe per vial

Kit sizes and National Drug Codes (NDC) are provided in Table 3.

Table 3: ZOLGENSMA Kit Sizes
Patient weight (kg) | 5.5 mL viala | 8.3 mL vialb | Total vials per kit | NDC number
2.6 – 3.0 | 0 | 2 | 2 | 71894-120-02
3.1 – 3.5 | 2 | 1 | 3 | 71894-121-03
3.6 – 4.0 | 1 | 2 | 3 | 71894-122-03
4.1 – 4.5 | 0 | 3 | 3 | 71894-123-03
4.6 – 5.0 | 2 | 2 | 4 | 71894-124-04
5.1 – 5.5 | 1 | 3 | 4 | 71894-125-04
5.6 – 6.0 | 0 | 4 | 4 | 71894-126-04
6.1 – 6.5 | 2 | 3 | 5 | 71894-127-05
6.6 – 7.0 | 1 | 4 | 5 | 71894-128-05
7.1 – 7.5 | 0 | 5 | 5 | 71894-129-05
7.6 – 8.0 | 2 | 4 | 6 | 71894-130-06
8.1 – 8.5 | 1 | 5 | 6 | 71894-131-06
8.6 – 9.0 | 0 | 6 | 6 | 71894-132-06
9.1 – 9.5 | 2 | 5 | 7 | 71894-133-07
9.6 – 10.0 | 1 | 6 | 7 | 71894-134-07
10.1 – 10.5 | 0 | 7 | 7 | 71894-135-07
10.6 – 11.0 | 2 | 6 | 8 | 71894-136-08
11.1 – 11.5 | 1 | 7 | 8 | 71894-137-08
11.6 – 12.0 | 0 | 8 | 8 | 71894-138-08
12.1 – 12.5 | 2 | 7 | 9 | 71894-139-09
12.6 – 13.0 | 1 | 8 | 9 | 71894-140-09
13.1 – 13.5 | 0 | 9 | 9 | 71894-141-09
13.6 – 14.0 | 2 | 8 | 10 | 71894-142-10
14.1 – 14.5 | 1 | 9 | 10 | 71894-143-10
14.6 – 15.0 | 0 | 10 | 10 | 71894-144-10
15.1 – 15.5 | 2 | 9 | 11 | 71894-145-11
15.6 – 16.0 | 1 | 10 | 11 | 71894-146-11
16.1 – 16.5 | 0 | 11 | 11 | 71894-147-11
16.6 – 17.0 | 2 | 10 | 12 | 71894-148-12
17.1 – 17.5 | 1 | 11 | 12 | 71894-149-12
17.6 – 18.0 | 0 | 12 | 12 | 71894-150-12
18.1 – 18.5 | 2 | 11 | 13 | 71894-151-13
18.6 – 19.0 | 1 | 12 | 13 | 71894-152-13
19.1 – 19.5 | 0 | 13 | 13 | 71894-153-13
19.6 – 20.0 | 2 | 12 | 14 | 71894-154-14
20.1 – 20.5 | 1 | 13 | 14 | 71894-155-14
20.6 – 21.0 | 0 | 14 | 14 | 71894-156-14
aVial nominal concentration is 2.0 × 10^13 vg/mL and contains an extractable volume of not less than 5.5 mL.
bVial nominal concentration is 2.0 × 10^13 vg/mL and contains an extractable volume of not less than 8.3 mL.

16.2 Storage and Handling

- Product is shipped and delivered frozen (≤ -60°C [-76°F]) in clear vials.
- Upon receipt, immediately place the kit in a refrigerator at 2°C to 8°C (36°F to 46°F).
- ZOLGENSMA is stable for 14 days from receipt when stored at 2°C to 8°C (36°F to 46°F).
- DO NOT REFREEZE.
- Must use within 14 days of receipt.

17 PATIENT COUNSELING INFORMATION

Acute Serious Liver Injury, Acute Liver Failure or Elevated Aminotransferases

Inform caregivers that ZOLGENSMA could increase liver enzyme levels and cause acute serious liver injury or acute liver failure, and death. Inform caregivers that patients will receive an oral corticosteroid medication before and after infusion with ZOLGENSMA, and will undergo regular blood tests to monitor liver function. Advise caregivers to contact their healthcare provider immediately if the patient’s skin and/or whites of the eyes appear yellowish, if the patient misses a dose of corticosteroid or vomits it up, or if the patient experiences a decrease in alertness [see Warnings and Precautions (5.1)].

Vaccination Before and After Infusion With ZOLGENSMA

Advise caregivers to consult with their healthcare provider to determine if adjustments to the patient’s vaccination schedule are necessary during corticosteroid use. Inform caregivers that where feasible, the vaccination schedule should be adjusted appropriately to accommodate treatment with corticosteroid. Prophylaxis against influenza and RSV is recommended and vaccination status should be up-to-date prior to ZOLGENSMA administration. Please consult your healthcare provider [see Drug Interactions (7)].

Systemic Immune Response

Caregivers should be aware that an infection (e.g., cold, flu, gastroenteritis, otitis media, bronchiolitis, etc.) before or after ZOLGENSMA infusion could lead to more serious complications. Caregivers and close contacts of patients should follow infection prevention practices (e.g., hand hygiene, coughing/sneezing etiquette, limiting potential contacts). Advise caregivers of the signs of a possible infection, such as coughing, wheezing, sneezing, runny nose, sore throat, or fever. Caregivers should contact their healthcare provider immediately if the patient experiences any symptoms suggestive of infection before or after ZOLGENSMA infusion [see Warnings and Precautions (5.2)].

Thrombocytopenia

Inform caregivers that ZOLGENSMA could decrease blood platelet count and increase the risk of bruising or bleeding. Inform caregivers that thrombocytopenia has been reported to generally occur within the first two weeks after ZOLGENSMA infusion. Advise caregivers to seek medical attention if the patient experiences unexpected bruising or bleeding [see Warnings and Precautions (5.3)].

Thrombotic Microangiopathy

Inform caregivers that ZOLGENSMA could decrease blood platelet and red blood cell counts, cause acute kidney injury, and increase the risk of bruising or bleeding, which may be indicative of TMA. Inform caregivers that TMA has been reported to generally occur within the first two weeks after ZOLGENSMA infusion. Advise caregivers to seek immediate medical attention if the patient experiences unexpected bruising or bleeding, seizures, or decreased urine output [see Warnings and Precautions (5.4)].

AAV Vector Integration and Risk of Tumorigenicity

Inform caregivers that there is a theoretical risk of tumorigenicity with AAV therapies such as ZOLGENSMA. Advise caregivers to contact their healthcare provider and Novartis Gene Therapies, Inc. (1-833-828-3947) if the patient who received ZOLGENSMA develops a tumor [see Warnings and Precautions (5.6)].

Vector Shedding

Temporary vector shedding of ZOLGENSMA occurs primarily through body waste. Advise caregivers on the proper handling of patient feces; recommended procedures include sealing disposable diapers in disposable trash bags and then discarding into regular trash. Provide instructions to caregivers and family members regarding proper hand hygiene when coming into direct contact with patient body waste. These precautions should be followed for one month after ZOLGENSMA infusion.

Infusion-Related Reactions

Inform caregivers that infusion-related reactions may occur during and after ZOLGENSMA infusion. Advise caregivers to seek immediate medical evaluation if signs and symptoms of infusion related reaction occur which may include rash, urticaria, vomiting, dyspnea, respiratory symptoms and/or alterations in heart rate and blood pressure [see Warnings and Precautions (5.7)].

Manufactured by, Packed by, Distributed by:

Novartis Gene Therapies, Inc.

2275 Half Day Road

Bannockburn, IL 60015 USA

U.S. License Number 2250

©2025 Novartis Gene Therapies, Inc.

T2025-04

PRINCIPAL DISPLAY PANEL

NDC 71894-110-01

onasemnogene abeparvovec-xioi
ZOLGENSMA®

Rx ONLY

Suspension for intravenous infusion.

See enclosed prescribing information
for dosage and directions for use.

Manufactured by Novartis Gene Therapies, Inc.
Bannockburn, IL 60015. US License No: 2250

5.5 mL

NOVARTIS

PRINCIPAL DISPLAY PANEL

NDC 71894-115-01

onasemnogene abeparvovec-xioi
ZOLGENSMA®

Rx ONLY

Suspension for intravenous infusion.

See enclosed prescribing information
for dosage and directions for use.

Manufactured by Novartis Gene Therapies, Inc.
Bannockburn, IL 60015. US License No: 2250

8.3 mL

NOVARTIS

PRINCIPAL DISPLAY PANEL

onasemnogene abeparvovec-xioi
ZOLGENSMA®

Rx ONLY

Suspension for intravenous infusion.

NOVARTIS

Manufactured by
Novartis Gene Therapies, Inc.
Bannockburn, IL 60015

US License No: 2250
©2021 Novartis Gene Therapies, Inc.